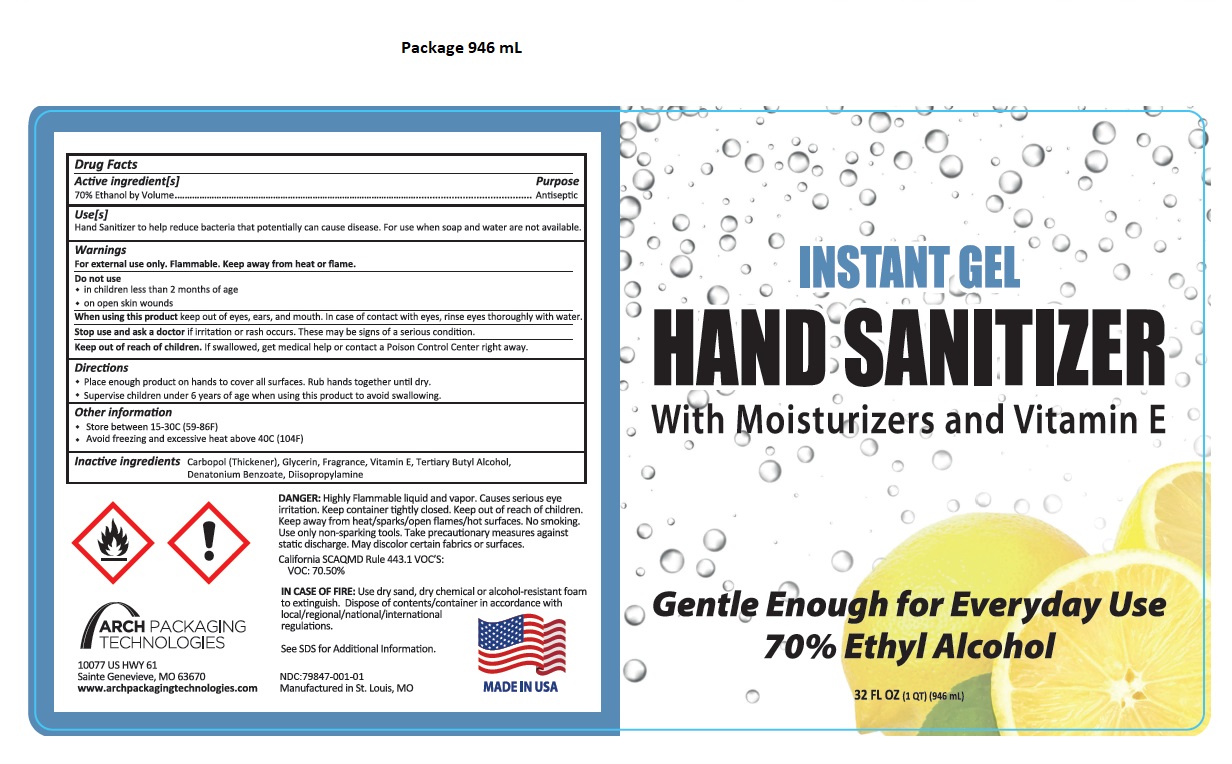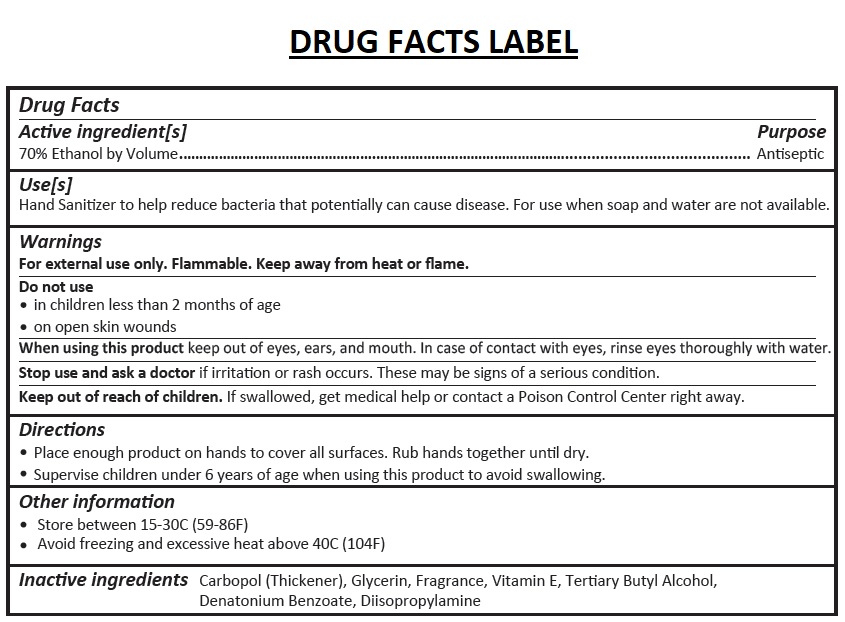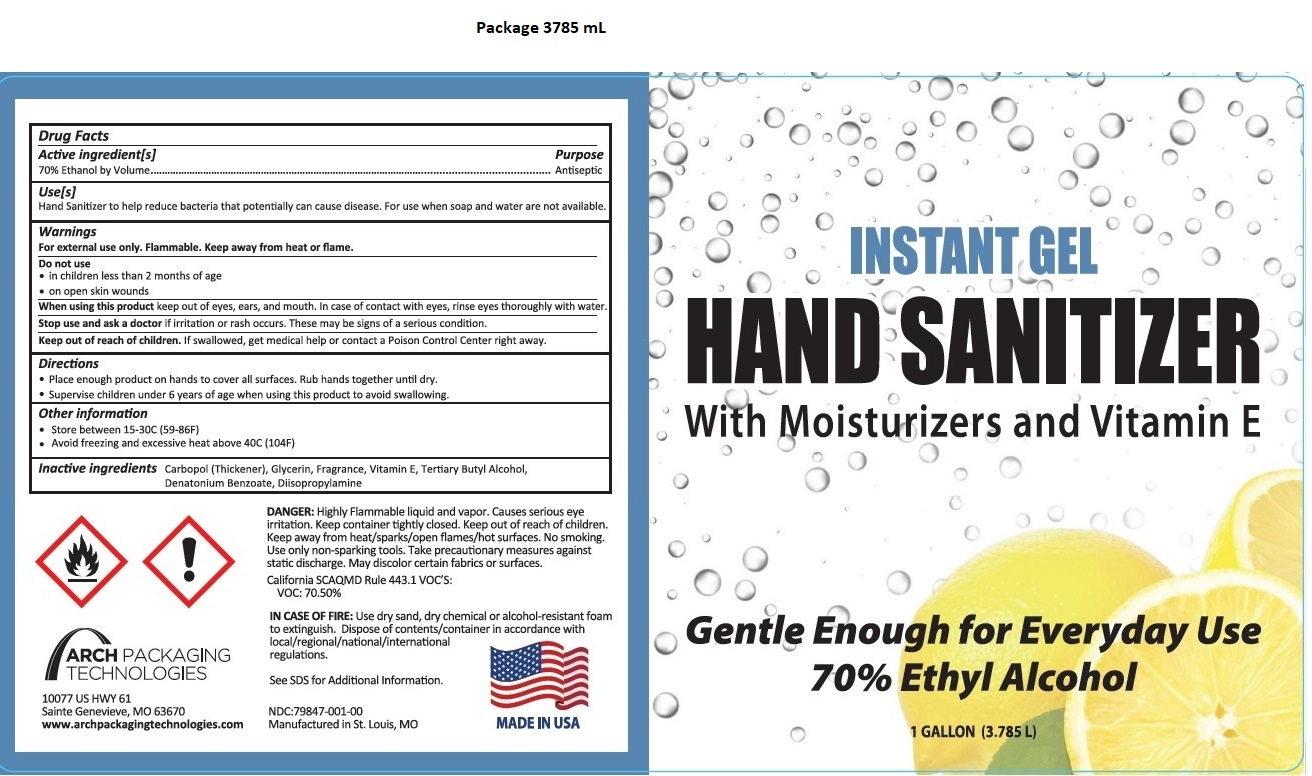 DRUG LABEL: Arch Packaging INSTANT Gel HAND SANITIZER
NDC: 79847-001 | Form: GEL
Manufacturer: Arch Packaging Technologies Llc
Category: otc | Type: HUMAN OTC DRUG LABEL
Date: 20200904

ACTIVE INGREDIENTS: ALCOHOL 70 mL/100 mL
INACTIVE INGREDIENTS: CARBOMER HOMOPOLYMER, UNSPECIFIED TYPE; GLYCERIN; .ALPHA.-TOCOPHEROL; BUTYL ALCOHOL; DENATONIUM BENZOATE; DIISOPROPYLAMINE

INSTANT GEL HAND SANITIZER

Active ingredient[s]

70% Ethanol by Volume

Purpose

Antiseptic

Use[s]

Hand Sanitizer to help reduce bacteria that potentially can cause disease. For use when soap and water are not available.

Warnings

For external use only. Flammable. Keep away from heat or flame.
Do not use
• in children less than 2 months of age
• on open skin wounds
When using this product keep out of eyes, ears, and mouth. In case of contact with eyes, rinse eyes thoroughly with water.
Stop use and ask a doctor if irritation or rash occurs. These may be signs of a serious condition.

Keep out of reach of children. If swallowed, get medical help or contact a Poison Control Center right away.

Directions

• Place enough product on hands to cover all surfaces. Rub hands together until dry.
• Supervise children under 6 years of age when using this product to avoid swallowing.

Other information

• Store between 15-30C (59-86F)
• Avoid freezing and excessive heat above 40C (104F)

Inactive ingredients

Carbopol (Thickener), Glycerin, Fragrance, Vitamin E, Tertiary Butyl Alcohol, Denatonium Benzoate, Diisopropylamine

With Moisturizers and Vitamin E

Gentle Enough for Everyday Use

70% Ethyl Alcohol

DANGER: Highly Flammable liquid and vapor. Causes serious eye irritation. Keep container tightly closed. Keep out of reach of children. Keep away from heat/sparks/open flames/hot surfaces. No smoking. Use only non-sparking tools. Take precautionary measures against static discharge. May discolor certain fabrics or surfaces.
California SCAQMD Rule 443.1 VOC’S:
VOC: 70.50%

IN CASE OF FIRE: Use dry sand, dry chemical or alcohol-resistant foam to extinguish. Dispose of contents/container in accordance with local/regional/national/international regulations.
See SDS for Additional Information

Manufactured in St. Louis, MO

ARCH PACKAGING TECHNOLOGIES

10077 US HWY 61
Sainte Genevieve, MO 63670
www.archpackagingtechnologies.com

MADE IN USA